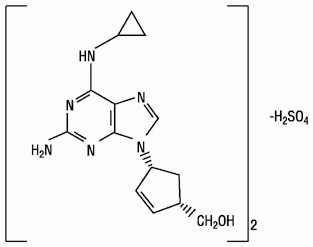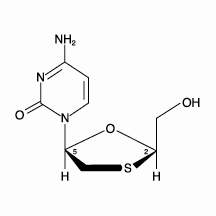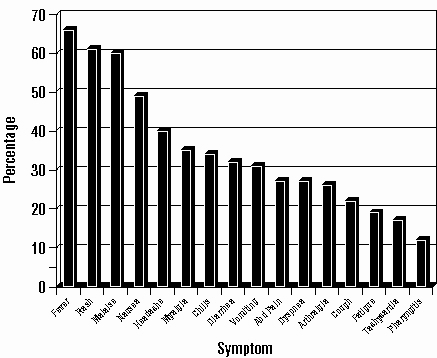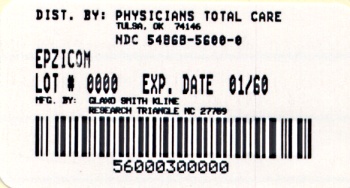 DRUG LABEL: EPZICOM
NDC: 54868-5600 | Form: TABLET, FILM COATED
Manufacturer: Physicians Total Care, Inc.
Category: prescription | Type: HUMAN PRESCRIPTION DRUG LABEL
Date: 20100701

ACTIVE INGREDIENTS: ABACAVIR SULFATE 600 mg/1 1; LAMIVUDINE 300 mg/1 1
INACTIVE INGREDIENTS: MAGNESIUM STEARATE; CELLULOSE, MICROCRYSTALLINE; SODIUM STARCH GLYCOLATE TYPE A POTATO; FD&C YELLOW NO. 6; HYPROMELLOSE; POLYETHYLENE GLYCOL 400; POLYSORBATE 80; TITANIUM DIOXIDE

EPZICOM®
(abacavir sulfate and lamivudine)
Tablets

WARNINGS

EPZICOM contains 2 nucleoside analogues (abacavir sulfate and lamivudine) and is intended only for patients whose regimen would otherwise include these 2 components.

Hypersensitivity Reactions: Serious and sometimes fatal hypersensitivity reactions have been associated with abacavir sulfate, a component of EPZICOM. Hypersensitivity to abacavir is a multi-organ clinical syndrome usually characterized by a sign or symptom in 2 or more of the following groups: (1) fever, (2) rash, (3) gastrointestinal (including nausea, vomiting, diarrhea, or abdominal pain), (4) constitutional (including generalized malaise, fatigue, or achiness), and (5) respiratory (including dyspnea, cough, or pharyngitis). Discontinue EPZICOM as soon as a hypersensitivity reaction is suspected.

Patients who carry the HLA-B*5701 allele are at high risk for experiencing a hypersensitivity reaction to abacavir. Prior to initiating therapy with abacavir, screening for the HLA-B*5701 allele is recommended; this approach has been found to decrease the risk of hypersensitivity reaction. Screening is also recommended prior to reinitiation of abacavir in patients of unknown HLA-B*5701 status who have previously tolerated abacavir. HLA-B*5701-negative patients may develop a suspected hypersensitivity reaction to abacavir; however, this occurs significantly less frequently than in HLA-B*5701-positive patients.

Regardless of HLA-B*5701 status, permanently discontinue EPZICOM if hypersensitivity cannot be ruled out, even when other diagnoses are possible.

Following a hypersensitivity reaction to abacavir, NEVER restart EPZICOM or any other abacavir-containing product because more severe symptoms can occur within hours and may include life-threatening hypotension and death.

Reintroduction of EPZICOM or any other abacavir-containing product, even in patients who have no identified history or unrecognized symptoms of hypersensitivity to abacavir therapy, can result in serious or fatal hypersensitivity reactions. Such reactions can occur within hours (see WARNINGS and PRECAUTIONS: Information for Patients).

Lactic Acidosis and Severe Hepatomegaly: Lactic acidosis and severe hepatomegaly with steatosis, including fatal cases, have been reported with the use of nucleoside analogues alone or in combination, including abacavir, lamivudine, and other antiretrovirals (see WARNINGS).

Exacerbations of Hepatitis B: Severe acute exacerbations of hepatitis B have been reported in patients who are co-infected with hepatitis B virus (HBV) and human immunodeficiency virus (HIV-1) and have discontinued lamivudine, which is one component of EPZICOM. Hepatic function should be monitored closely with both clinical and laboratory follow-up for at least several months in patients who discontinue EPZICOM and are co-infected with HIV-1 and HBV. If appropriate, initiation of anti-hepatitis B therapy may be warranted (see WARNINGS).

DESCRIPTION

EPZICOM:

EPZICOM Tablets contain the following 2 synthetic nucleoside analogues: abacavir sulfate (ZIAGEN®, also a component of TRIZIVIR®) and lamivudine (also known as EPIVIR® or 3TC) with inhibitory activity against HIV-1.

EPZICOM Tablets are for oral administration. Each orange, film-coated tablet contains the active ingredients 600 mg of abacavir as abacavir sulfate and 300 mg of lamivudine, and the inactive ingredients magnesium stearate, microcrystalline cellulose, and sodium starch glycolate. The tablets are coated with a film (OPADRY® orange YS-1-13065-A) that is made of FD&C Yellow No. 6, hypromellose, polyethylene glycol 400, polysorbate 80, and titanium dioxide.

Abacavir Sulfate:

The chemical name of abacavir sulfate is (1S,cis)-4-[2-amino-6-(cyclopropylamino)-9H-purin-9-yl]-2-cyclopentene-1-methanol sulfate (salt) (2:1). Abacavir sulfate is the enantiomer with 1S, 4R absolute configuration on the cyclopentene ring. It has a molecular formula of (C14H18N6O)2•H2SO4 and a molecular weight of 670.76 daltons. It has the following structural formula:

Abacavir sulfate is a white to off-white solid with a solubility of approximately 77 mg/mL in distilled water at 25°C.

In vivo, abacavir sulfate dissociates to its free base, abacavir. All dosages for abacavir sulfate are expressed in terms of abacavir.

Lamivudine:

The chemical name of lamivudine is (2R,cis)-4-amino-1-(2-hydroxymethyl-1,3-oxathiolan-5-yl)-(1H)-pyrimidin-2-one. Lamivudine is the (-)enantiomer of a dideoxy analogue of cytidine. Lamivudine has also been referred to as (-)2′,3′-dideoxy, 3′-thiacytidine. It has a molecular formula of C8H11N3O3S and a molecular weight of 229.3 daltons. It has the following structural formula:

Lamivudine is a white to off-white crystalline solid with a solubility of approximately 70 mg/mL in water at 20°C.

MICROBIOLOGY

Mechanism of Action:

Abacavir is a carbocyclic synthetic nucleoside analogue. Abacavir is converted by cellular enzymes to the active metabolite, carbovir triphosphate (CBV-TP), an analogue of deoxyguanosine-5′-triphosphate (dGTP). CBV-TP inhibits the activity of HIV-1 reverse transcriptase (RT) both by competing with the natural substrate dGTP and by its incorporation into viral DNA. The lack of a 3′-OH group in the incorporated nucleotide analogue prevents the formation of the 5′ to 3′ phosphodiester linkage essential for DNA chain elongation, and therefore, the viral DNA growth is terminated. CBV-TP is a weak inhibitor of cellular DNA polymerases α, β, and γ.

Lamivudine is a synthetic nucleoside analogue. Intracellularly lamivudine is phosphorylated to its active 5′-triphosphate metabolite, lamivudine triphosphate (3TC-TP). The principal mode of action of 3TC-TP is inhibition of RT via DNA chain termination after incorporation of the nucleotide analogue. CBV-TP and 3TC-TP are weak inhibitors of cellular DNA polymerases α, β, and γ.

Antiviral Activity:

Abacavir:

The antiviral activity of abacavir against HIV-1 was evaluated against a T-cell tropic laboratory strain HIV-1IIIB in lymphoblastic cell lines, a monocyte/macrophage tropic laboratory strain HIV-1BaL in primary monocytes/macrophages, and clinical isolates in peripheral blood mononuclear cells. The concentration of drug necessary to effect viral replication by 50 percent (EC50) ranged from 3.7 to 5.8 μM (1 μM = 0.28 mcg/mL) and 0.07 to 1.0 μM against HIV-1IIIB and HIV-1BaL, respectively, and was 0.26 ± 0.18 μM against 8 clinical isolates. The EC50 values of abacavir against different HIV-1 clades (A-G) ranged from 0.0015 to 1.05 μM, and against HIV-2 isolates, from 0.024 to 0.49 μM. Ribavirin (50 μM) had no effect on the anti–HIV-1 activity of abacavir in cell culture.

Lamivudine:

The antiviral activity of lamivudine against HIV-1 was assessed in a number of cell lines (including monocytes and fresh human peripheral blood lymphocytes) using standard susceptibility assays. EC50 values were in the range of 0.003 to 15 μM (1 μM = 0.23 mcg/mL). HIV-1 from therapy-naive subjects with no amino acid substitutions associated with resistance gave median EC50 values of 0.429 µM (range: 0.200 to 2.007 µM) from Virco (n = 92 baseline samples from COLA40263) and 2.35 µM (1.37 to 3.68 µM) from Monogram Biosciences (n = 135 baseline samples from ESS30009). The EC50 values of lamivudine against different HIV-1 clades (A-G) ranged from 0.001 to 0.120 µM, and against HIV-2 isolates from 0.003 to 0.120 μM in peripheral blood mononuclear cells. Ribavirin (50 μM) decreased the anti–HIV-1 activity of lamivudine by 3.5 fold in MT-4 cells.

The combination of abacavir and lamivudine has demonstrated antiviral activity in cell culture against non-subtype B isolates and HIV-2 isolates with equivalent antiviral activity as for subtype B isolates. Abacavir/lamivudine had additive to synergistic activity in cell culture in combination with the nucleoside reverse transcriptase inhibitors (NRTIs) emtricitabine, stavudine, tenofovir, zalcitabine, zidovudine; the non-nucleoside reverse transcriptase inhibitors (NNRTIs) delavirdine, efavirenz, nevirapine; the protease inhibitors (PIs) amprenavir, indinavir, lopinavir, nelfinavir, ritonavir, saquinavir; or the fusion inhibitor, enfuvirtide. Ribavirin, used in combination with interferon for the treatment of HCV infection, decreased the anti-HIV-1 potency of abacavir/lamivudine reproducibly by 2- to 6-fold in cell culture.

Resistance:

HIV-1 isolates with reduced susceptibility to the combination of abacavir and lamivudine have been selected in cell culture and have also been obtained from patients failing abacavir/lamivudine-containing regimens. Genotypic characterization of abacavir/lamivudine-resistant viruses selected in cell culture identified amino acid substitutions M184V/I, K65R, L74V, and Y115F in HIV-1 RT.

Genotypic analysis of isolates selected in cell culture and recovered from abacavir-treated patients demonstrated that amino acid substitutions K65R, L74V, Y115F, and M184V/I in HIV-1 RT contributed to abacavir resistance. Genotypic analysis of isolates selected in cell culture and recovered from lamivudine-treated patients showed that the resistance was due to a specific amino acid substitution in HIV-1 RT at codon 184 changing the methionine to either isoleucine or valine (M184V/I). In a study of therapy-naive adults receiving ZIAGEN 600 mg once daily (n = 384) or 300 mg twice daily (n = 386) in a background regimen of lamivudine 300 mg and efavirenz 600 mg once daily (Study CNA30021), the incidence of virologic failure at 48 weeks was similar between the 2 groups (11% in both arms). Genotypic (n = 38) and phenotypic analyses (n = 35) of virologic failure isolates from this study showed that the RT substitutions that emerged during abacavir/lamivudine once-daily and twice-daily therapy were K65R, L74V, Y115F, and M184V/I. The abacavir- and lamivudine-associated resistance substitution M184V/I was the most commonly observed substitution in virologic failure isolates from patients receiving abacavir/lamivudine once daily (56%, 10/18) and twice daily (40%, 8/20).

Thirty-nine percent (7/18) of the isolates from patients who experienced virologic failure in the abacavir once-daily arm had a >2.5-fold decrease in abacavir susceptibility with a median-fold decrease of 1.3 (range: 0.5 to 11) compared with 29% (5/17) of the failure isolates in the twice-daily arm with a median-fold decrease of 0.92 (range: 0.7 to 13). Fifty-six percent (10/18) of the virologic failure isolates in the once-daily abacavir group compared with 41% (7/17) of the failure isolates in the twice-daily abacavir group had a >2.5-fold decrease in lamivudine susceptibility with median-fold changes of 81 (range 0.79 to >116) and 1.1 (range 0.68 to >116) in the once-daily and twice-daily abacavir arms, respectively.

Cross-Resistance:

Cross-resistance has been observed among NRTIs. Viruses containing abacavir and lamivudine resistance-associated amino acid substitutions, namely, K65R, L74V, M184V, and Y115F, exhibit cross-resistance to didanosine, emtricitabine, lamivudine, tenofovir, and zalcitabine in cell culture and in patients. The K65R substitution can confer resistance to abacavir, didanosine, emtricitabine, lamivudine, stavudine, tenofovir, and zalcitabine; the L74V substitution can confer resistance to abacavir, didanosine, and zalcitabine; and the M184V substitution can confer resistance to abacavir, didanosine, emtricitabine, lamivudine, and zalcitabine.

The combination of abacavir/lamivudine has demonstrated decreased susceptibility to viruses with the substitutions K65R with or without the M184V/I substitution, viruses with L74V plus the M184V/I substitution, and viruses with thymidine analog mutations (TAMs: M41L, D67N, K70R, L210W, T215Y/F, K219 E/R/H/Q/N) plus M184V. An increasing number of TAMs is associated with a progressive reduction in abacavir susceptibility.

CLINICAL PHARMACOLOGY

Pharmacokinetics in Adults:

EPZICOM:

In a single-dose, 3-way crossover bioavailability study of 1 EPZICOM Tablet versus 2 ZIAGEN Tablets (2 x 300 mg) and 2 EPIVIR Tablets (2 x 150 mg) administered simultaneously in healthy subjects (n = 25), there was no difference in the extent of absorption, as measured by the area under the plasma concentration-time curve (AUC) and maximal peak concentration (Cmax), of each component.

Abacavir:

Following oral administration, abacavir is rapidly absorbed and extensively distributed. After oral administration of a single dose of 600 mg of abacavir in 20 patients, Cmax was 4.26 ± 1.19 mcg/mL (mean ± SD) and AUC∞ was 11.95 ± 2.51 mcg•hr/mL. Binding of abacavir to human plasma proteins is approximately 50% and was independent of concentration. Total blood and plasma drug-related radioactivity concentrations are identical, demonstrating that abacavir readily distributes into erythrocytes. The primary routes of elimination of abacavir are metabolism by alcohol dehydrogenase to form the 5′-carboxylic acid and glucuronyl transferase to form the 5′-glucuronide.

Lamivudine:

Following oral administration, lamivudine is rapidly absorbed and extensively distributed. After multiple-dose oral administration of lamivudine 300 mg once daily for 7 days to 60 healthy volunteers, steady-state Cmax (Cmax,ss) was 2.04 ± 0.54 mcg/mL (mean ± SD) and the 24-hour steady-state AUC (AUC24,ss) was 8.87 ± 1.83 mcg•hr/mL. Binding to plasma protein is low. Approximately 70% of an intravenous dose of lamivudine is recovered as unchanged drug in the urine. Metabolism of lamivudine is a minor route of elimination. In humans, the only known metabolite is the trans-sulfoxide metabolite (approximately 5% of an oral dose after 12 hours).

The steady-state pharmacokinetic properties of the EPIVIR 300-mg Tablet once daily for 7 days compared with the EPIVIR 150-mg Tablet twice daily for 7 days were assessed in a crossover study in 60 healthy volunteers. EPIVIR 300 mg once daily resulted in lamivudine exposures that were similar to EPIVIR 150 mg twice daily with respect to plasma AUC24,ss; however, Cmax,ss was 66% higher and the trough value was 53% lower compared with the 150-mg twice-daily regimen. Intracellular lamivudine triphosphate exposures in peripheral blood mononuclear cells were also similar with respect to AUC24,ss and Cmax24,ss; however, trough values were lower compared with the 150-mg twice-daily regimen. Inter-subject variability was greater for intracellular lamivudine triphosphate concentrations versus lamivudine plasma trough concentrations. The clinical significance of observed differences for both plasma lamivudine concentrations and intracellular lamivudine triphosphate concentrations is not known.

In humans, abacavir and lamivudine are not significantly metabolized by cytochrome P450 enzymes.

The pharmacokinetic properties of abacavir and lamivudine in fasting patients are summarized in Table 1.

Table 1. Pharmacokinetic Parameters* for Abacavir and Lamivudine in Adults
Parameter | Abacavir |  | Lamivudine
Oral bioavailability (%) | 86 ± 25 | n = 6 | 86 ± 16 | n = 12
Apparent volume of distribution (L/kg) | 0.86 ± 0.15 | n = 6 | 1.3 ± 0.4 | n = 20
Systemic clearance (L/hr/kg) | 0.80 ± 0.24 | n = 6 | 0.33 ± 0.06 | n = 20
Renal clearance (L/hr/kg) | .007 ± .008 | n = 6 | 0.22 ± 0.06 | n = 20
Elimination half-life (hr) | 1.45 ± 0.32 | n = 20 | 5 to 7†
* Data presented as mean ± standard deviation except where noted.
† Approximate range.

Effect of Food on Absorption of EPZICOM:

EPZICOM may be administered with or without food. Administration with a high-fat meal in a single-dose bioavailability study resulted in no change in AUClast, AUC∞, and Cmax for lamivudine. Food did not alter the extent of systemic exposure to abacavir (AUC∞), but the rate of absorption (Cmax) was decreased approximately 24% compared with fasted conditions (n = 25). These results are similar to those from previous studies of the effect of food on abacavir and lamivudine tablets administered separately.

Special Populations:

Impaired Renal Function:

EPZICOM: Because lamivudine requires dose adjustment in the presence of renal insufficiency, EPZICOM is not recommended for use in patients with creatinine clearance <50 mL/min (see PRECAUTIONS).

Impaired Hepatic Function:

EPZICOM: Abacavir is contraindicated in patients with moderate to severe hepatic impairment and dose reduction is required in patients with mild hepatic impairment. Because EPZICOM is a fixed-dose combination and cannot be dose adjusted, EPZICOM is contraindicated for patients with hepatic impairment.

Pregnancy:

See PRECAUTIONS: Pregnancy.

Abacavir and Lamivudine: No data are available on the pharmacokinetics of abacavir or lamivudine during pregnancy.

Nursing Mothers:

See PRECAUTIONS: Nursing Mothers.

Abacavir: No data are available on the pharmacokinetics of abacavir in nursing mothers.

Lamivudine: Samples of breast milk obtained from 20 mothers receiving lamivudine monotherapy (300 mg twice daily) or combination therapy (150 mg lamivudine twice daily and 300 mg zidovudine twice daily) had measurable concentrations of lamivudine.

Pediatric Patients:

EPZICOM: The pharmacokinetics of EPZICOM in pediatric patients are under investigation. There are insufficient data at this time to recommend a dose (see PRECAUTIONS: Pediatric Use).

Geriatric Patients:

The pharmacokinetics of abacavir and lamivudine have not been studied in patients over 65 years of age.

Gender:

Abacavir: A population pharmacokinetic analysis in HIV-1-infected male (n = 304) and female (n = 67) patients showed no gender differences in abacavir AUC normalized for lean body weight.

Lamivudine: A pharmacokinetic study in healthy male (n = 12) and female (n = 12) subjects showed no gender differences in lamivudine AUC∞ normalized for body weight.

Race:

Abacavir: There are no significant differences between blacks and Caucasians in abacavir pharmacokinetics.

Lamivudine: There are no significant racial differences in lamivudine pharmacokinetics.

Drug Interactions:

See PRECAUTIONS: Drug Interactions. The drug interactions described are based on studies conducted with the individual nucleoside analogues. In humans, abacavir and lamivudine are not significantly metabolized by cytochrome P450 enzymes nor do they inhibit or induce this enzyme system; therefore, it is unlikely that clinically significant drug interactions will occur with drugs metabolized through these pathways.

Abacavir:

Fifteen HIV-1-infected patients were enrolled in a crossover-designed drug interaction study evaluating single doses of abacavir (600 mg), lamivudine (150 mg), and zidovudine (300 mg) alone or in combination. Analysis showed no clinically relevant changes in the pharmacokinetics of abacavir with the addition of lamivudine or zidovudine or the combination of lamivudine and zidovudine. Lamivudine exposure (AUC decreased 15%) and zidovudine exposure (AUC increased 10%) did not show clinically relevant changes with concurrent abacavir.

In a study of 11 HIV-1-infected patients receiving methadone-maintenance therapy (40 mg and 90 mg daily), with 600 mg of ZIAGEN twice daily (twice the currently recommended dose), oral methadone clearance increased 22% (90% CI: 6% to 42%). This alteration will not result in a methadone dose modification in the majority of patients; however, an increased methadone dose may be required in a small number of patients.

Lamivudine:

No clinically significant alterations in lamivudine or zidovudine pharmacokinetics were observed in 12 asymptomatic HIV-1-infected adult patients given a single dose of zidovudine (200 mg) in combination with multiple doses of lamivudine (300 mg q 12 hr). Lamivudine pharmacokinetics are not significantly affected by abacavir.

Table 2. Effect of Coadministered Drugs on Abacavir and Lamivudine AUC*
Note: ROUTINE DOSE MODIFICATION OF ABACAVIR AND LAMIVUDINE IS NOT WARRANTED WITH COADMINISTRATION OF THE FOLLOWING DRUGS.
Drugs That May Alter Abacavir Blood Concentrations
Coadministered; Drug and Dose | Abacavir Dose | n | Abacavir; Concentrations |  | Concentration of Coadministered Drug
Coadministered; Drug and Dose | Abacavir Dose | n | AUC | Variability | Concentration of Coadministered Drug
Ethanol; 0.7 g/kg | Single 600 mg | 24 | ↑41% | 90% CI:; 35% to 48% | ↔
Drugs That May Alter Lamivudine Blood Concentrations
Coadministered; Drug and Dose | Lamivudine Dose | n | Lamivudine; Concentrations |  |  | Concentration of Coadministered Drug
Coadministered; Drug and Dose | Lamivudine Dose | n | AUC | Variability |  | Concentration of Coadministered Drug
Nelfinavir; 750 mg q 8 hr x 7 to 10 days | Single 150 mg | 11 | ↑10% | 95% CI:; 1% to 20% |  | ↔
Trimethoprim 160 mg/; Sulfamethoxazole; 800 mg daily x 5 days | Single 300 mg | 14 | ↑43% | 90% CI:; 32% to 55% |  | ↔
↑ = Increase; ↔ = no significant change; AUC = area under the concentration versus time curve; CI = confidence interval.
* See PRECAUTIONS: Drug Interactions for additional information on drug interactions.

Ribavirin:

In vitro data indicate ribavirin reduces phosphorylation of lamivudine, stavudine, and zidovudine. However, no pharmacokinetic (e.g., plasma concentrations or intracellular triphosphorylated active metabolite concentrations) or pharmacodynamic (e.g., loss of HIV-1/HCV virologic suppression) interaction was observed when ribavirin and lamivudine (n = 18), stavudine (n = 10), or zidovudine (n = 6) were coadministered as part of a multi-drug regimen to HIV-1/HCV co-infected patients (see WARNINGS).

INDICATIONS AND USAGE

EPZICOM Tablets, in combination with other antiretroviral agents, are indicated for the treatment of HIV-1 infection.

Additional important information on the use of EPZICOM for treatment of HIV-1 infection:

- EPZICOM is one of multiple products containing abacavir. Before starting EPZICOM, review medical history for prior exposure to any abacavir-containing product in order to avoid reintroduction in a patient with a history of hypersensitivity to abacavir.
- In one controlled study (CNA30021), more patients taking ZIAGEN 600 mg once daily had severe hypersensitivity reactions compared with patients taking ZIAGEN 300 mg twice daily.
- As part of a triple-drug regimen, EPZICOM Tablets are recommended for use with antiretroviral agents from different pharmacological classes and not with other nucleoside/nucleotide reverse transcriptase inhibitors.

See WARNINGS, ADVERSE REACTIONS, and Description of Clinical Studies.

Description of Clinical Studies:

EPZICOM:

There have been no clinical trials conducted with EPZICOM (see CLINICAL PHARMACOLOGY for information about bioequivalence of EPZICOM). One EPZICOM Tablet given once daily is an alternative regimen to EPIVIR Tablets 300 mg once daily plus ZIAGEN Tablets 2 x 300 mg once daily as a component of antiretroviral therapy.

The following study was conducted with the individual components of EPZICOM.

Therapy-Naive Adults:

CNA30021 was an international, multi-center, double-blind, controlled study in which 770 HIV-1-infected, therapy-naive adults were randomized and received either ZIAGEN 600 mg once daily or ZIAGEN 300 mg twice daily, both in combination with EPIVIR 300 mg once daily and efavirenz 600 mg once daily. The double-blind treatment duration was at least 48 weeks. Study participants had a mean age of 37 years, were: male (81%), Caucasian (54%), black (27%), and American Hispanic (15%). The median baseline CD4+ cell count was 262 cells/mm^3 (range: 21 to 918 cells/mm^3) and the median baseline plasma HIV-1 RNA was 4.89 log10 copies/mL (range: 2.60 to 6.99 log10 copies/mL).

The outcomes of randomized treatment are provided in Table 3.

Table 3. Outcomes of Randomized Treatment Through Week 48 (CNA30021)
Outcome | ZIAGEN 600 mg q.d.; plus EPIVIR plus; Efavirenz; (n = 384) | ZIAGEN 300 mg b.i.d.; plus EPIVIR plus; Efavirenz; (n = 386)
Responder* | 64% (71%) | 65% (72%)
Virologic failure† | 11% (5%) | 11% (5%)
Discontinued due to adverse reactions | 13% | 11%
Discontinued due to other reasons‡ | 11% | 13%
* Patients achieved and maintained confirmed HIV-1 RNA <50 copies/mL (<400 copies/mL) through Week 48 (Roche AMPLICOR Ultrasensitive HIV-1 MONITOR® standard test version 1.0).
† Includes viral rebound, failure to achieve confirmed <50 copies/mL (<400 copies/mL) by Week 48, and insufficient viral load response.
‡ Includes consent withdrawn, lost to follow-up, protocol violations, clinical progression, and other.

After 48 weeks of therapy, the median CD4+ cell count increases from baseline were 188 cells/mm^3 in the group receiving ZIAGEN 600 mg once daily and 200 cells/mm^3 in the group receiving ZIAGEN 300 mg twice daily. Through Week 48, 6 subjects (2%) in the group receiving ZIAGEN 600 mg once daily (4 CDC classification C events and 2 deaths) and 10 subjects (3%) in the group receiving ZIAGEN 300 mg twice daily (7 CDC classification C events and 3 deaths) experienced clinical disease progression. None of the deaths were attributed to study medications.

CONTRAINDICATIONS

EPZICOM Tablets are contraindicated in patients with previously demonstrated hypersensitivity to abacavir or to any other component of the product (see WARNINGS). NEVER restart EPZICOM or any other abacavir-containing product following a hypersensitivity reaction to abacavir, regardless of HLA-B*5701 status (see WARNINGS, PRECAUTIONS, and ADVERSE REACTIONS).

EPZICOM Tablets are contraindicated in patients with hepatic impairment (see CLINICAL PHARMACOLOGY).

WARNINGS

Hypersensitivity Reaction:

Serious and sometimes fatal hypersensitivity reactions have been associated with EPZICOM and other abacavir-containing products.Patients who carry the HLA-B*5701 allele are at high risk for experiencing a hypersensitivity reaction to abacavir. Prior to initiating therapy with abacavir, screening for the HLA-B*5701 allele is recommended; this approach has been found to decrease the risk of a hypersensitivity reaction. Screening is also recommended prior to reinitiation of abacavir in patients of unknown HLA-B*5701 status who have previously tolerated abacavir. For HLA-B*5701-positive patients, treatment with an abacavir-containing regimen is not recommended and should be considered only with close medical supervision and under exceptional circumstances when the potential benefit outweighs the risk.

HLA-B*5701-negative patients may develop a hypersensitivity reaction to abacavir; however, this occurs significantly less frequently than in HLA-B*5701-positive patients. Regardless of HLA-B*5701 status, permanently discontinue EPZICOM if hypersensitivity cannot be ruled out, even when other diagnoses are possible.

Important information on signs and symptoms of hypersensitivity, as well as clinical management, is presented below.

Signs and Symptoms of Hypersensitivity

Hypersensitivity to abacavir is a multi-organ clinical syndrome usually characterized by a sign or symptom in 2 or more of the following groups.

Group 1: Fever

Group 2: Rash

Group 3: Gastrointestinal (including nausea, vomiting, diarrhea, or abdominal pain)

Group 4: Constitutional (including generalized malaise, fatigue, or achiness)

Group 5: Respiratory (including dyspnea, cough, or pharyngitis)

Hypersensitivity to abacavir following the presentation of a single sign or symptom has been reported infrequently.

Hypersensitivity to abacavir was reported in approximately 8% of 2,670 patients (n = 206) in 9 clinical trials (range: 2% to 9%) with enrollment from November 1999 to February 2002. Data on time to onset and symptoms of suspected hypersensitivity were collected on a detailed data collection module. The frequencies of symptoms are shown in Figure 1. Symptoms usually appeared within the first 6 weeks of treatment with abacavir, although the reaction may occur at any time during therapy. Median time to onset was 9 days; 89% appeared within the first 6 weeks; 95% of patients reported symptoms from 2 or more of the 5 groups listed above.

Figure 1: Hypersensitivity-Related Symptoms Reported with ≥10% Frequency in Clinical Trials (n = 206 Patients)

Other less common signs and symptoms of hypersensitivity include lethargy, myolysis, edema, abnormal chest x-ray findings (predominantly infiltrates, which can be localized), and paresthesia.

Anaphylaxis, liver failure, renal failure, hypotension, adult respiratory distress syndrome, respiratory failure, and death have occurred in association with hypersensitivity reactions. In one study, 4 patients (11%) receiving ZIAGEN 600 mg once daily experienced hypotension with a hypersensitivity reaction compared with 0 patients receiving ZIAGEN 300 mg twice daily.

Physical findings associated with hypersensitivity to abacavir in some patients include lymphadenopathy, mucous membrane lesions (conjunctivitis and mouth ulcerations), and rash. The rash usually appears maculopapular or urticarial, but may be variable in appearance. There have been reports of erythema multiforme. Hypersensitivity reactions have occurred without rash.

Laboratory abnormalities associated with hypersensitivity to abacavir in some patients include elevated liver function tests, elevated creatine phosphokinase, elevated creatinine, and lymphopenia.

Clinical Management of Hypersensitivity:

Discontinue EPZICOM as soon as a hypersensitivity reaction is suspected. To minimize the risk of a life-threatening hypersensitivity reaction, permanently discontinue EPZICOM if hypersensitivity cannot be ruled out, even when other diagnoses are possible (e.g., acute onset respiratory diseases such as pneumonia, bronchitis, pharyngitis, or influenza; gastroenteritis; or reactions to other medications).

Following a hypersensitivity reaction to abacavir, NEVER restart EPZICOM or any other abacavir-containing product because more severe symptoms can occur within hours and may include life-threatening hypotension and death.

When therapy with EPZICOM has been discontinued for reasons other than symptoms of a hypersensitivity reaction, and if reinitiation of EPZICOM or any other abacavir-containing product is under consideration, carefully evaluate the reason for discontinuation of EPZICOM to ensure that the patient did not have symptoms of a hypersensitivity reaction. If the patient is of unknown HLA-B*5701 status, screening for the allele is recommended prior to reinitiation of EPZICOM.

If hypersensitivity cannot be ruled out, DO NOT reintroduce EPZICOM or any other abacavir-containing product. Even in the absence of the HLA-B*5701 allele, it is important to permanently discontinue abacavir and not rechallenge with abacavir if a hypersensitivity reaction cannot be ruled out on clinical grounds, due to the potential for a severe or even fatal reaction.

If symptoms consistent with hypersensitivity are not identified, reintroduction can be undertaken with continued monitoring for symptoms of a hypersensitivity reaction. Make patients aware that a hypersensitivity reaction can occur with reintroduction of EPZICOM or any other abacavir-containing product and that reintroduction of EPZICOM or introduction of any other abacavir-containing product needs to be undertaken only if medical care can be readily accessed by the patient or others.

Risk Factor:

HLA-B*5701 Allele: Studies have shown that carriage of the HLA-B*5701 allele is associated with a significantly increased risk of a hypersensitivity reaction to abacavir.

CNA106030 (PREDICT-1), a randomized, double-blind study, evaluated the clinical utility of prospective HLA-B*5701 screening on the incidence of abacavir hypersensitivity reaction in abacavir-naive HIV-1-infected adults (n = 1,650). In this study, use of pre-therapy screening for the HLA-B*5701 allele and exclusion of subjects with this allele reduced the incidence of clinically suspected abacavir hypersensitivity reactions from 7.8% (66/847) to 3.4% (27/803). Based on this study, it is estimated that 61% of patients with the HLA-B*5701 allele will develop a clinically suspected hypersensitivity reaction during the course of abacavir treatment compared with 4% of patients who do not have the HLA-B*5701 allele.

Screening for carriage of the HLA-B*5701 allele is recommended prior to initiating treatment with abacavir. Screening is also recommended prior to reinitiation of abacavir in patients of unknown HLA-B*5701 status who have previously tolerated abacavir. For HLA-B*5701-positive patients, initiating or reinitiating treatment with an abacavir-containing regimen is not recommended and should be considered only with close medical supervision and under exceptional circumstances where potential benefit outweighs the risk.

Skin patch testing is used as a research tool and should not be used to aid in the clinical diagnosis of abacavir hypersensitivity.

In any patient treated with abacavir, the clinical diagnosis of hypersensitivity reaction must remain the basis of clinical decision-making. Even in the absence of the HLA-B*5701 allele, it is important to permanently discontinue abacavir and not rechallenge with abacavir if a hypersensitivity reaction cannot be ruled out on clinical grounds, due to the potential for a severe or even fatal reaction.

Abacavir Hypersensitivity Reaction Registry:

An Abacavir Hypersensitivity Registry has been established to facilitate reporting of hypersensitivity reactions and collection of information on each case. Physicians should register patients by calling 1-800-270-0425.

Lactic Acidosis/Severe Hepatomegaly With Steatosis:

Lactic acidosis and severe hepatomegaly with steatosis, including fatal cases, have been reported with the use of nucleoside analogues alone or in combination, including abacavir and lamivudine and other antiretrovirals. A majority of these cases have been in women. Obesity and prolonged nucleoside exposure may be risk factors. Particular caution should be exercised when administering EPZICOM to any patient with known risk factors for liver disease; however, cases have also been reported in patients with no known risk factors. Treatment with EPZICOM should be suspended in any patient who develops clinical or laboratory findings suggestive of lactic acidosis or pronounced hepatotoxicity (which may include hepatomegaly and steatosis even in the absence of marked transaminase elevations).

Posttreatment Exacerbations of Hepatitis:

In clinical trials in non-HIV-1-infected patients treated with lamivudine for chronic HBV, clinical and laboratory evidence of exacerbations of hepatitis have occurred after discontinuation of lamivudine. These exacerbations have been detected primarily by serum ALT elevations in addition to re-emergence of HBV DNA. Although most events appear to have been self-limited, fatalities have been reported in some cases. Similar events have been reported from post-marketing experience after changes from lamivudine-containing HIV-1 treatment regimens to non-lamivudine-containing regimens in patients infected with both HIV-1 and HBV. The causal relationship to discontinuation of lamivudine treatment is unknown. Patients should be closely monitored with both clinical and laboratory follow-up for at least several months after stopping treatment. There is insufficient evidence to determine whether re-initiation of lamivudine alters the course of posttreatment exacerbations of hepatitis.

Use With Interferon- and Ribavirin-Based Regimens:

In vitro studies have shown ribavirin can reduce the phosphorylation of pyrimidine nucleoside analogues such as lamivudine, a component of EPZICOM. Although no evidence of a pharmacokinetic or pharmacodynamic interaction (e.g., loss of HIV-1/HCV virologic suppression) was seen when ribavirin was coadministered with lamivudine in HIV-1/HCV co-infected patients (see CLINICAL PHARMACOLOGY: Drug Interactions), hepatic decompensation (some fatal) has occurred in HIV-1/HCV co-infected patients receiving combination antiretroviral therapy for HIV-1 and interferon alfa with or without ribavirin. Patients receiving interferon alfa with or without ribavirin and EPZICOM should be closely monitored for treatment-associated toxicities, especially hepatic decompensation. Discontinuation of EPZICOM should be considered as medically appropriate. Dose reduction or discontinuation of interferon alfa, ribavirin, or both should also be considered if worsening clinical toxicities are observed, including hepatic decompensation (e.g., Childs Pugh >6) (see the complete prescribing information for interferon and ribavirin).

Other:

EPZICOM contains fixed doses of 2 nucleoside analogues, abacavir and lamivudine, and should not be administered concomitantly with other abacavir-containing and/or lamivudine-containing products (ZIAGEN, EPIVIR, COMBIVIR®, or TRIZIVIR).

The complete prescribing information for all agents being considered for use with EPZICOM should be consulted before combination therapy with EPZICOM is initiated.

PRECAUTIONS

Therapy-Experienced Patients:

Abacavir:

In clinical trials, patients with prolonged prior NRTI exposure or who had HIV-1 isolates that contained multiple mutations conferring resistance to NRTIs had limited response to abacavir. The potential for cross-resistance between abacavir and other NRTIs should be considered when choosing new therapeutic regimens in therapy-experienced patients (see MICROBIOLOGY: Cross-Resistance).

Patients With HIV-1 and Hepatitis B Virus Co-infection:

Lamivudine:

Safety and efficacy of lamivudine have not been established for treatment of chronic hepatitis B in patients dually infected with HIV-1 and HBV. In non-HIV-1-infected patients treated with lamivudine for chronic hepatitis B, emergence of lamivudine-resistant HBV has been detected and has been associated with diminished treatment response (see EPIVIR-HBV package insert for additional information). Emergence of hepatitis B virus variants associated with resistance to lamivudine has also been reported in HIV-1-infected patients who have received lamivudine-containing antiretroviral regimens in the presence of concurrent infection with hepatitis B virus.

Patients With Impaired Renal Function:

EPZICOM:

Since EPZICOM is a fixed-dose tablet and the dosage of the individual components cannot be altered, patients with creatinine clearance <50 mL/min should not receive EPZICOM.

Patients With Impaired Hepatic Function:

EPZICOM:

EPZICOM is contraindicated in patients with hepatic impairment since it is a fixed-dose tablet and the dosage of the individual components cannot be altered.

Immune reconstitution syndrome has been reported in patients treated with combination antiretroviral therapy, including EPZICOM. During the initial phase of combination antiretroviral treatment, patients whose immune system responds may develop an inflammatory response to indolent or residual opportunistic infections (such as Mycobacterium avium infection, cytomegalovirus, Pneumocystis jirovecii pneumonia [PCP], or tuberculosis), which may necessitate further evaluation and treatment.

Fat Redistribution:

Redistribution/accumulation of body fat including central obesity, dorsocervical fat enlargement (buffalo hump), peripheral wasting, facial wasting, breast enlargement, and “cushingoid appearance” have been observed in patients receiving antiretroviral therapy. The mechanism and long-term consequences of these events are currently unknown. A causal relationship has not been established.

Myocardial Infarction:

In a published prospective, observational, epidemiological study designed to investigate the rate of myocardial infarction in patients on combination antiretroviral therapy, the use of abacavir within the previous 6 months was correlated with an increased risk of myocardial infarction (MI).^1 In a sponsor-conducted pooled analysis of clinical trials, no excess risk of MI was observed in abacavir-treated subjects as compared with control subjects. In totality, the available data from the observational cohort and from clinical trials are inconclusive.

As a precaution, the underlying risk of coronary heart disease should be considered when prescribing antiretroviral therapies, including abacavir, and action taken to minimize all modifiable risk factors (e.g., hypertension, hyperlipidemia, diabetes mellitus, and smoking).

Information for Patients:

Abacavir:

Hypersensitivity Reaction: Inform patients:

- that a Medication Guide and Warning Card summarizing the symptoms of the abacavir hypersensitivity reaction and other product information will be dispensed by the pharmacist with each new prescription and refill of EPZICOM, and encourage the patient to read the Medication Guide and Warning Card every time to obtain any new information that may be present about EPZICOM. (The complete text of the Medication Guide is reprinted at the end of this document.)
- to carry the Warning Card with them.
- how to identify a hypersensitivity reaction (see WARNINGS and MEDICATION GUIDE).
- that if they develop symptoms consistent with a hypersensitivity reaction they should call their doctor right away to determine if they should stop taking EPZICOM.
- that a hypersensitivity reaction can worsen and lead to hospitalization or death if EPZICOM is not immediately discontinued.
- to not restart EPZICOM or any other abacavir-containing product following a hypersensitivity reaction because more severe symptoms can occur within hours and may include life-threatening hypotension and death.
- that a hypersensitivity reaction is usually reversible if it is detected promptly and EPZICOM is stopped right away.
- that if they have interrupted EPZICOM for reasons other than symptoms of hypersensitivity (for example, those who have an interruption in drug supply), a serious or fatal hypersensitivity reaction may occur with reintroduction of abacavir.
- that in one study, more severe hypersensitivity reactions were seen when ZIAGEN was dosed 600 mg once daily.
- to not restart EPZICOM or any other abacavir-containing product without medical consultation and that restarting abacavir needs to be undertaken only if medical care can be readily accessed by the patient or others.

Lamivudine:

Patients co-infected with HIV-1 and HBV should be informed that deterioration of liver disease has occurred in some cases when treatment with lamivudine was discontinued. Patients should be advised to discuss any changes in regimen with their physician.

EPZICOM:

Inform patients that some HIV-1 medicines, including EPZICOM, can cause a rare, but serious condition called lactic acidosis with liver enlargement (hepatomegaly).

EPZICOM is not a cure for HIV-1 infection and patients may continue to experience illnesses associated with HIV-1 infection, including opportunistic infections. Patients should remain under the care of a physician when using EPZICOM. Advise patients that the use of EPZICOM has not been shown to reduce the risk of transmission of HIV-1 to others through sexual contact or blood contamination.

Inform patients that redistribution or accumulation of body fat may occur in patients receiving antiretroviral therapy and that the cause and long-term health effects of these conditions are not known at this time.

EPZICOM Tablets are for oral ingestion only.

Patients should be advised of the importance of taking EPZICOM exactly as it is prescribed.

Drug Interactions:

EPZICOM:

No clinically significant changes to pharmacokinetic parameters were observed for abacavir or lamivudine when administered together.

Abacavir:

Abacavir has no effect on the pharmacokinetic properties of ethanol. Ethanol decreases the elimination of abacavir causing an increase in overall exposure (see CLINICAL PHARMACOLOGY: Drug Interactions).

The addition of methadone has no clinically significant effect on the pharmacokinetic properties of abacavir. In a study of 11 HIV-1-infected patients receiving methadone-maintenance therapy (40 mg and 90 mg daily), with 600 mg of ZIAGEN twice daily (twice the currently recommended dose), oral methadone clearance increased 22% (90% CI: 6% to 42%). This alteration will not result in a methadone dose modification in the majority of patients; however, an increased methadone dose may be required in a small number of patients.

Lamivudine:

Trimethoprim (TMP) 160 mg/sulfamethoxazole (SMX) 800 mg once daily has been shown to increase lamivudine exposure (AUC). No change in dose of either drug is recommended. The effect of higher doses of TMP/SMX on lamivudine pharmacokinetics has not been investigated (see CLINICAL PHARMACOLOGY).

Lamivudine and zalcitabine may inhibit the intracellular phosphorylation of one another. Therefore, use of EPZICOM in combination with zalcitabine is not recommended.

See CLINICAL PHARMACOLOGY for additional drug interactions.

Carcinogenesis, Mutagenesis, Impairment of Fertility:

Carcinogenicity:

Abacavir: Abacavir was administered orally at 3 dosage levels to separate groups of mice and rats in 2-year carcinogenicity studies. Results showed an increase in the incidence of malignant and non-malignant tumors. Malignant tumors occurred in the preputial gland of males and the clitoral gland of females of both species, and in the liver of female rats. In addition, non-malignant tumors also occurred in the liver and thyroid gland of female rats. These observations were made at systemic exposures in the range of 6 to 32 times the human exposure at the recommended dose.

Lamivudine: Long-term carcinogenicity studies with lamivudine in mice and rats showed no evidence of carcinogenic potential at exposures up to 10 times (mice) and 58 times (rats) those observed in humans at the recommended therapeutic dose for HIV-1 infection.

It is not known how predictive the results of rodent carcinogenicity studies may be for humans.

Mutagenicity:

Abacavir: Abacavir induced chromosomal aberrations both in the presence and absence of metabolic activation in an in vitro cytogenetic study in human lymphocytes. Abacavir was mutagenic in the absence of metabolic activation, although it was not mutagenic in the presence of metabolic activation in an L5178Y mouse lymphoma assay. Abacavir was clastogenic in males and not clastogenic in females in an in vivo mouse bone marrow micronucleus assay. Abacavir was not mutagenic in bacterial mutagenicity assays in the presence and absence of metabolic activation.

Lamivudine: Lamivudine was mutagenic in an L5178Y mouse lymphoma assay and clastogenic in a cytogenetic assay using cultured human lymphocytes. Lamivudine was not mutagenic in a microbial mutagenicity assay, in an in vitro cell transformation assay, in a rat micronucleus test, in a rat bone marrow cytogenetic assay, and in an assay for unscheduled DNA synthesis in rat liver.

Impairment of Fertility:

Abacavir or lamivudine induced no adverse effects on the mating performance or fertility of male and female rats at doses producing systemic exposure levels approximately 8 or 130 times, respectively, higher than those in humans at the recommended dose based on body surface area comparisons.

Pregnancy:

Pregnancy Category C. There are no adequate and well-controlled studies of EPZICOM in pregnant women. Reproduction studies with abacavir and lamivudine have been performed in animals (see Abacavir and Lamivudine sections below). EPZICOM should be used during pregnancy only if the potential benefits outweigh the risks.

Abacavir:

Studies in pregnant rats showed that abacavir is transferred to the fetus through the placenta. Fetal malformations (increased incidences of fetal anasarca and skeletal malformations) and developmental toxicity (depressed fetal body weight and reduced crown-rump length) were observed in rats at a dose which produced 35 times the human exposure, based on AUC. Embryonic and fetal toxicities (increased resorptions, decreased fetal body weights) and toxicities to the offspring (increased incidence of stillbirth and lower body weights) occurred at half of the above-mentioned dose in separate fertility studies conducted in rats. In the rabbit, no developmental toxicity and no increases in fetal malformations occurred at doses that produced 8.5 times the human exposure at the recommended dose based on AUC.

Lamivudine:

Studies in pregnant rats showed that lamivudine is transferred to the fetus through the placenta. Reproduction studies with orally administered lamivudine have been performed in rats and rabbits at doses producing plasma levels up to approximately 35 times that for the recommended adult HIV dose. No evidence of teratogenicity due to lamivudine was observed. Evidence of early embryolethality was seen in the rabbit at exposure levels similar to those observed in humans, but there was no indication of this effect in the rat at exposure levels up to 35 times those in humans.

Antiretroviral Pregnancy Registry:

To monitor maternal-fetal outcomes of pregnant women exposed to EPZICOM or other antiretroviral agents, an Antiretroviral Pregnancy Registry has been established. Physicians are encouraged to register patients by calling 1-800-258-4263.

Nursing Mothers:

The Centers for Disease Control and Prevention recommend that HIV-1-infected mothers not breastfeed their infants to avoid risking postnatal transmission of HIV-1 infection.

Abacavir:

Abacavir is secreted into the milk of lactating rats.

Lamivudine:

Lamivudine is excreted in human breast milk and into the milk of lactating rats.

Because of both the potential for HIV-1 transmission and the potential for serious adverse reactions in nursing infants, mothers should be instructed not to breastfeed if they are receiving EPZICOM.

Pediatric Use:

Safety and effectiveness of EPZICOM in pediatric patients have not been established.

Geriatric Use:

Clinical studies of abacavir and lamivudine did not include sufficient numbers of patients aged 65 and over to determine whether they respond differently from younger patients. In general, dose selection for an elderly patient should be cautious, reflecting the greater frequency of decreased hepatic, renal, or cardiac function, and of concomitant disease or other drug therapy. EPZICOM is not recommended for patients with impaired renal function or impaired hepatic function (see PRECAUTIONS and DOSAGE AND ADMINISTRATION).

ADVERSE REACTIONS

Abacavir:

Hypersensitivity Reaction:

Serious and sometimes fatal hypersensitivity reactions have been associated with abacavir sulfate, a component of EPZICOM.

In one study, once-daily dosing of ZIAGEN was associated with more severe hypersensitivity reactions (see WARNINGS and PRECAUTIONS: Information for Patients).

Therapy-Naive Adults:

Treatment-emergent clinical adverse reactions (rated by the investigator as moderate or severe) with a ≥5% frequency during therapy with ZIAGEN 600 mg once daily or ZIAGEN 300 mg twice daily, both in combination with lamivudine 300 mg once daily and efavirenz 600 mg once daily are listed in Table 4.

Table 4. Treatment-Emergent (All Causality) Adverse Reactions of at Least Moderate Intensity (Grades 2-4, ≥5% Frequency) in Therapy-Naive Adults (CNA30021) Through 48 Weeks of Treatment
Adverse Event | ZIAGEN 600 mg q.d.; plus EPIVIR plus Efavirenz; (n = 384) | ZIAGEN 300 mg b.i.d.; plus EPIVIR plus Efavirenz; (n = 386)
Drug hypersensitivity*† | 9% | 7%
Insomnia | 7% | 9%
Depression/Depressed mood | 7% | 7%
Headache/Migraine | 7% | 6%
Fatigue/Malaise | 6% | 8%
Dizziness/Vertigo | 6% | 6%
Nausea | 5% | 6%
Diarrhea* | 5% | 6%
Rash | 5% | 5%
Pyrexia | 5% | 3%
Abdominal pain/gastritis | 4% | 5%
Abnormal dreams | 4% | 5%
Anxiety | 3% | 5%
* Patients receiving ZIAGEN 600 mg once daily, experienced a significantly higher incidence of severe drug hypersensitivity reactions and severe diarrhea compared with patients who received ZIAGEN 300 mg twice daily. Five percent (5%) of patients receiving ZIAGEN 600 mg once daily had severe drug hypersensitivity reactions compared with 2% of patients receiving ZIAGEN 300 mg twice daily. Two percent (2%) of patients receiving ZIAGEN 600 mg once daily had severe diarrhea while none of the patients receiving ZIAGEN 300 mg twice daily had this event.
† Study CNA30024 was a multi-center, double-blind, controlled study in which 649 HIV-1-infected, therapy-naive adults were randomized and received either ZIAGEN (300 mg twice daily), EPIVIR (150 mg twice daily), and efavirenz (600 mg once daily) or zidovudine (300 mg twice daily), EPIVIR (150 mg twice daily), and efavirenz (600 mg once daily). CNA30024 used double-blind ascertainment of suspected hypersensitivity reactions. During the blinded portion of the study, suspected hypersensitivity to abacavir was reported by investigators in 9% of 324 patients in the abacavir group and 3% of 325 patients in the zidovudine group.

Laboratory Abnormalities:

Laboratory abnormalities observed in clinical studies of ZIAGEN were anemia, neutropenia, liver function test abnormalities, and elevations of CPK, blood glucose, and triglycerides. Additional laboratory abnormalities observed in clinical studies of EPIVIR were thrombocytopenia and elevated levels of bilirubin, amylase, and lipase.

The frequencies of treatment-emergent laboratory abnormalities were comparable between treatment groups in Study CNA30021.

Other Adverse Events:

In addition to adverse reactions listed above, other adverse events observed in the expanded access program for abacavir were pancreatitis and increased GGT.

Observed During Clinical Practice:

The following reactions have been identified during post-approval use of abacavir and lamivudine. Because they are reported voluntarily from a population of unknown size, estimates of frequency cannot be made. These events have been chosen for inclusion due to a combination of their seriousness, frequency of reporting, or potential causal connection to abacavir and/or lamivudine.

Abacavir:

Cardiovascular: Myocardial infarction.

Skin: Suspected Stevens-Johnson syndrome (SJS) and toxic epidermal necrolysis (TEN) have been reported in patients receiving abacavir primarily in combination with medications known to be associated with SJS and TEN, respectively. Because of the overlap of clinical signs and symptoms between hypersensitivity to abacavir and SJS and TEN, and the possibility of multiple drug sensitivities in some patients, abacavir should be discontinued and not restarted in such cases.

There have also been reports of erythema multiforme with abacavir use.

Abacavir and Lamivudine:

Body as a Whole: Redistribution/accumulation of body fat (see PRECAUTIONS: Fat Redistribution).

Digestive: Stomatitis.

Endocrine and Metabolic: Hyperglycemia.

General: Weakness.

Hemic and Lymphatic: Aplastic anemia, anemia (including pure red cell aplasia and severe anemias progressing on therapy), lymphadenopathy, splenomegaly.

Hepatic and Pancreatic: Lactic acidosis and hepatic steatosis, pancreatitis, posttreatment exacerbation of hepatitis B (see WARNINGS).

Hypersensitivity: Sensitization reactions (including anaphylaxis), urticaria.

Musculoskeletal: Muscle weakness, CPK elevation, rhabdomyolysis.

Nervous: Paresthesia, peripheral neuropathy, seizures.

Respiratory: Abnormal breath sounds/wheezing.

Skin: Alopecia, erythema multiforme, Stevens-Johnson syndrome.

OVERDOSAGE

Abacavir:

There is no known antidote for abacavir. It is not known whether abacavir can be removed by peritoneal dialysis or hemodialysis.

Lamivudine:

One case of an adult ingesting 6 grams of lamivudine was reported; there were no clinical signs or symptoms noted and hematologic tests remained normal. It is not known whether lamivudine can be removed by peritoneal dialysis or hemodialysis.

DOSAGE AND ADMINISTRATION

A Medication Guide and Warning Card that provide information about recognition of hypersensitivity reactions should be dispensed with each new prescription and refill. To facilitate reporting of hypersensitivity reactions and collection of information on each case, an Abacavir Hypersensitivity Registry has been established. Physicians should register patients by calling 1-800-270-0425.

The recommended oral dose of EPZICOM for adults is one tablet daily, in combination with other antiretroviral agents (see INDICATIONS AND USAGE: Description of Clinical Studies, PRECAUTIONS, MICROBIOLOGY, and CLINICAL PHARMACOLOGY).

EPZICOM can be taken with or without food.

Dose Adjustment:

Because it is a fixed-dose tablet, EPZICOM should not be prescribed for patients requiring dosage adjustment such as those with creatinine clearance <50 mL/min, those with hepatic impairment, or those experiencing dose-limiting adverse events. Use of EPIVIR Oral Solution and ZIAGEN Oral Solution may be considered.

HOW SUPPLIED

EPZICOM is available as tablets. Each tablet contains 600 mg of abacavir as abacavir sulfate and 300 mg of lamivudine. The tablets are orange, film-coated, modified capsule-shaped, and debossed with GS FC2 on one side with no markings on the reverse side. They are packaged as follows:

NDC 54868-5600-0 | Bottles of 30

Store at 25°C (77°F); excursions permitted to 15° to 30°C (59° to 86°F) (see USP Controlled Room Temperature).

ANIMAL TOXICOLOGY

Myocardial degeneration was found in mice and rats following administration of abacavir for 2 years. The systemic exposures were equivalent to 7 to 24 times the expected systemic exposure in humans. The clinical relevance of this finding has not been determined.

REFERENCE

1. Data Collection on Adverse Events of Anti-HIV Drugs (D:A:D) Study Group. Lancet. 2008;371 (9622):1417-1426.

MEDICATION GUIDE

EPZICOM® (ep' zih com) Tablets

Generic name: abacavir (uH-BACK-ah-veer) sulfate and lamivudine (la-MIV-yoo-deen)

Read the Medication Guide that comes with EPZICOM before you start taking it and each time you get a refill because there may be new information. This information does not take the place of talking to your doctor about your medical condition or your treatment. Be sure to carry your EPZICOM Warning Card with you at all times.

What is the most important information I should know about EPZICOM?

- Serious Allergic Reaction to Abacavir. EPZICOM contains abacavir (also contained in ZIAGEN® and TRIZIVIR®). Patients taking EPZICOM may have a serious allergic reaction (hypersensitivity reaction) that can cause death. Your risk of this allergic reaction is much higher if you have a gene variation called HLA-B*5701 than if you do not. Your doctor can determine with a blood test if you have this gene variation. If you get a symptom from 2 or more of the following groups while taking EPZICOM, call your doctor right away to determine if you should stop taking this medicine.
   | Symptom(s)
  Group 1 | Fever
  Group 2 | Rash
  Group 3 | Nausea, vomiting, diarrhea, abdominal (stomach area) pain
  Group 4 | Generally ill feeling, extreme tiredness, or achiness
  Group 5 | Shortness of breath, cough, sore throat

A list of these symptoms is on the Warning Card your pharmacist gives you. Carry this Warning Card with you.

If you stop EPZICOM because of an allergic reaction, NEVER take EPZICOM (abacavir sulfate and lamivudine) or any other abacavir-containing medicine (ZIAGEN and TRIZIVIR) again. If you take EPZICOM or any other abacavir-containing medicine again after you have had an allergic reaction, WITHIN HOURS you may get life-threatening symptoms that may include very low blood pressure or death.

If you stop EPZICOM for any other reason, even for a few days, and you are not allergic to EPZICOM, talk with your doctor before taking it again. Taking EPZICOM again can cause a serious allergic or life-threatening reaction, even if you never had an allergic reaction to it before. If your doctor tells you that you can take EPZICOM again, start taking it when you are around medical help or people who can call a doctor if you need one.

- Lactic Acidosis. Some human immunodeficiency virus (HIV) medicines, including EPZICOM, can cause a rare but serious condition called lactic acidosis with liver enlargement (hepatomegaly). Nausea and tiredness that don't get better may be symptoms of lactic acidosis. In some cases this condition can cause death. Women, overweight people, and people who have taken HIV medicines like EPZICOM for a long time have a higher chance of getting lactic acidosis and liver enlargement. Lactic acidosis is a medical emergency and must be treated in the hospital.
- Worsening of hepatitis B virus (HBV) infection. Patients with HBV infection, who take EPZICOM and then stop it, may get “flare-ups” of their hepatitis. “Flare-up” is when the disease suddenly returns in a worse way than before. If you have HBV infection, your doctor should closely monitor your liver function for several months after stopping EPZICOM. You may need to take anti-HBV medicines.
- Use with interferon- and ribavirin-based regimens. Worsening of liver disease (sometimes resulting in death) has occurred in patients infected with both HIV and hepatitis C virus who are taking anti-HIV medicines and are also being treated for hepatitis C with interferon with or without ribavirin. If you are taking EPZICOM as well as interferon with or without ribavirin and you experience side effects, be sure to tell your doctor.

EPZICOM can have other serious side effects. Be sure to read the section below entitled "What are the possible side effects of EPZICOM?"

What is EPZICOM?

EPZICOM is a prescription medicine used to treat HIV infection. EPZICOM includes 2 medicines: abacavir (ZIAGEN) and lamivudine or 3TC (EPIVIR®). See the end of this Medication Guide for a complete list of ingredients in EPZICOM. Both of these medicines are called nucleoside analogue reverse transcriptase inhibitors (NRTIs). When used together, they help lower the amount of HIV in your blood. This helps to keep your immune system as healthy as possible so that it can help fight infection.

Different combinations of medicines are used to treat HIV infection. You and your doctor should discuss which combination of medicines is best for you.

- EPZICOM does not cure HIV infection or AIDS. We do not know if EPZICOM will help you live longer or have fewer of the medical problems that people get with HIV or AIDS. It is very important that you see your doctor regularly while you are taking EPZICOM.
- EPZICOM does not lower the risk of passing HIV to other people through sexual contact, sharing needles, or being exposed to your blood. For your health and the health of others, it is important to always practice safe sex by using a latex or polyurethane condom or other barrier method to lower the chance of sexual contact with semen, vaginal secretions, or blood. Never use or share dirty needles.

Who should not take EPZICOM?

Do not take EPZICOM if you:

- have ever had a serious allergic reaction (a hypersensitivity reaction) to EPZICOM or any other medicine that has abacavir as one of its ingredients (TRIZIVIR and ZIAGEN). See the end of this Medication Guide for a complete list of ingredients in EPZICOM.
- have a liver that does not function properly.
- are less than 18 years of age.

Before starting EPZICOM tell your doctor about all of your medical conditions, including if you:

- have been tested and know whether or not you have a particular gene variation called HLA-B*5701.
- are pregnant or planning to become pregnant. We do not know if EPZICOM will harm your unborn child. You and your doctor will need to decide if EPZICOM is right for you. If you use EPZICOM while you are pregnant, talk to your doctor about how you can be on the Antiviral Pregnancy Registry for EPZICOM.
- are breastfeeding. Some of the ingredients in EPZICOM can be passed to your baby in your breast milk. It is not known if they could harm your baby. Also, mothers with HIV should not breastfeed because HIV can be passed to the baby in the breast milk.
- have liver problems including hepatitis B virus infection.
- have kidney problems.
- have heart problems, smoke, or suffer from diseases that increase your risk of heart disease such as high blood pressure, high cholesterol, or diabetes.

Tell your doctor about all the medicines you take, including prescription and nonprescription medicines, vitamins, and herbal supplements. Especially tell your doctor if you take any of the following medicines*:

- methadone
- HIVID® (zalcitabine, ddC)
- EPIVIR or EPIVIR-HBV® (lamivudine, 3TC), ZIAGEN (abacavir sulfate), COMBIVIR® (lamivudine and zidovudine), or TRIZIVIR (abacavir sulfate, lamivudine, and zidovudine).

How should I take EPZICOM?

- Take EPZICOM by mouth exactly as your doctor prescribes it. The usual dose is 1 tablet once a day. Do not skip doses.
- You can take EPZICOM with or without food.
- If you miss a dose of EPZICOM, take the missed dose right away. Then, take the next dose at the usual time.
- Do not let your EPZICOM run out.
- Starting EPZICOM again can cause a serious allergic or life-threatening reaction, even if you never had an allergic reaction to it before. If you run out of EPZICOM even for a few days, you must ask your doctor if you can start EPZICOM again. If your doctor tells you that you can take EPZICOM again, start taking it when you are around medical help or people who can call a doctor if you need one.
- If you stop your anti-HIV drugs, even for a short time, the amount of virus in your blood may increase and the virus may become harder to treat.
- If you take too much EPZICOM, call your doctor or poison control center right away.

What should I avoid while taking EPZICOM?

- Do not take EPIVIR (lamivudine, 3TC), COMBIVIR (lamivudine and zidovudine), ZIAGEN (abacavir sulfate), or TRIZIVIR (abacavir sulfate, lamivudine, and zidovudine) while taking EPZICOM. Some of these medicines are already in EPZICOM.
- Do not take zalcitabine (HIVID, ddC) while taking EPZICOM.

Avoid doing things that can spread HIV infection, as EPZICOM does not stop you from passing the HIV infection to others.

- Do not share needles or other injection equipment.
- Do not share personal items that can have blood or body fluids on them, like toothbrushes and razor blades.
- Do not have any kind of sex without protection. Always practice safe sex by using a latex or polyurethane condom or other barrier method to lower the chance of sexual contact with semen, vaginal secretions, or blood.
- Do not breastfeed. EPZICOM can be passed to babies in breast milk and could harm the baby. Also, mothers with HIV should not breastfeed because HIV can be passed to the baby in the breast milk.

What are the possible side effects of EPZICOM?

EPZICOM can cause the following serious side effects:

- Serious allergic reaction that can cause death. (See "What is the most important information I should know about EPZICOM?" at the beginning of this Medication Guide.)
- Lactic acidosis with liver enlargement (hepatomegaly) that can cause death. (See "What is the most important information I should know about EPZICOM?" at the beginning of this Medication Guide.)
- Worsening of HBV infection. (See "What is the most important information I should know about EPZICOM?" at the beginning of this Medication Guide.)
- Changes in immune system. When you start taking HIV medicines, your immune system may get stronger and could begin to fight infections that have been hidden in your body, such as pneumonia, herpes virus, or tuberculosis. If you have new symptoms after starting your HIV medicines, be sure to tell your doctor.
- Changes in body fat. These changes have happened in patients taking antiretroviral medicines like EPZICOM. The changes may include an increased amount of fat in the upper back and neck (“buffalo hump”), breast, and around the back, chest, and stomach area. Loss of fat from the legs, arms, and face may also happen. The cause and long-term health effects of these conditions are not known.

Some HIV medicines including EPZICOM may increase your risk of heart attack. If you have heart problems, smoke, or suffer from diseases that increase your risk of heart disease such as high blood pressure, high cholesterol, or diabetes, tell your doctor.

The most common side effects with EPZICOM are trouble sleeping, depression, headache, tiredness, dizziness, nausea, diarrhea, rash, fever, stomach pain, abnormal dreams, and anxiety. Most of these side effects did not cause people to stop taking EPZICOM.

This list of side effects is not complete. Call your doctor for medical advice about side effects. You may report side effects to FDA at 1-800-FDA-1088.

How should I store EPZICOM?

- Store EPZICOM at room temperature between 59° to 86°F (15° to 30°C).
- Keep EPZICOM and all medicines out of the reach of children.

General information for safe and effective use of EPZICOM

Medicines are sometimes prescribed for conditions that are not mentioned in Medication Guides. Do not use EPZICOM for a condition for which it was not prescribed. Do not give EPZICOM to other people, even if they have the same symptoms that you have. It may harm them.

This Medication Guide summarizes the most important information about EPZICOM. If you would like more information, talk with your doctor. You can ask your doctor or pharmacist for the information that is written for healthcare professionals or call 1-888-825-5249.

What are the ingredients in EPZICOM?

Active ingredients: abacavir sulfate and lamivudine

Inactive ingredients: Each film-coated EPZICOM Tablet contains the inactive ingredients magnesium stearate, microcrystalline cellulose, and sodium starch glycolate. The tablets are coated with a film (OPADRY® orange YS-1-13065-A) that is made of FD&C Yellow No. 6, hypromellose, polyethylene glycol 400, polysorbate 80, and titanium dioxide.

This Medication Guide has been approved by the US Food and Drug Administration.

March 2009
EPZ:2MG

COMBIVIR, EPIVIR, EPZICOM, TRIZIVIR, and ZIAGEN are registered trademarks of GlaxoSmithKline.

* The brands listed are trademarks of their respective owners and are not trademarks of GlaxoSmithKline. The makers of these brands are not affiliated with and do not endorse GlaxoSmithKline or its products.

GlaxoSmithKline
Research Triangle Park, NC 27709

Lamivudine is manufactured under agreement from
Shire Pharmaceuticals Group plc
Basingstoke, UK

©2009, GlaxoSmithKline. All rights reserved.

March 2009
EPZ:2PI

Relabeling of "Additional Barcode Label" by:
Physicians Total Care, Inc.
Tulsa, OK 74146

PACKAGE LABEL

PRINCIPAL DISPLAY PANEL

EPZICOM®

(abacavir sulfate and lamivudine)

600 mg 300 mg

TABLETS

30 Tablets

Notice to Authorized Dispenser: Each time EPZICOM is dispensed, give the patient a Medication Guide and Warning Card from the carton.

Rx only

Each tablet contains 600 mg of abacavir as abacavir sulfate and 300 mg of lamivudine.

Store at 25oC (77oF); excursions permitted to 15o to 30oC (59o to 86oF) (see USP Controlled Room Temperature).

See prescribing information for dosage information.